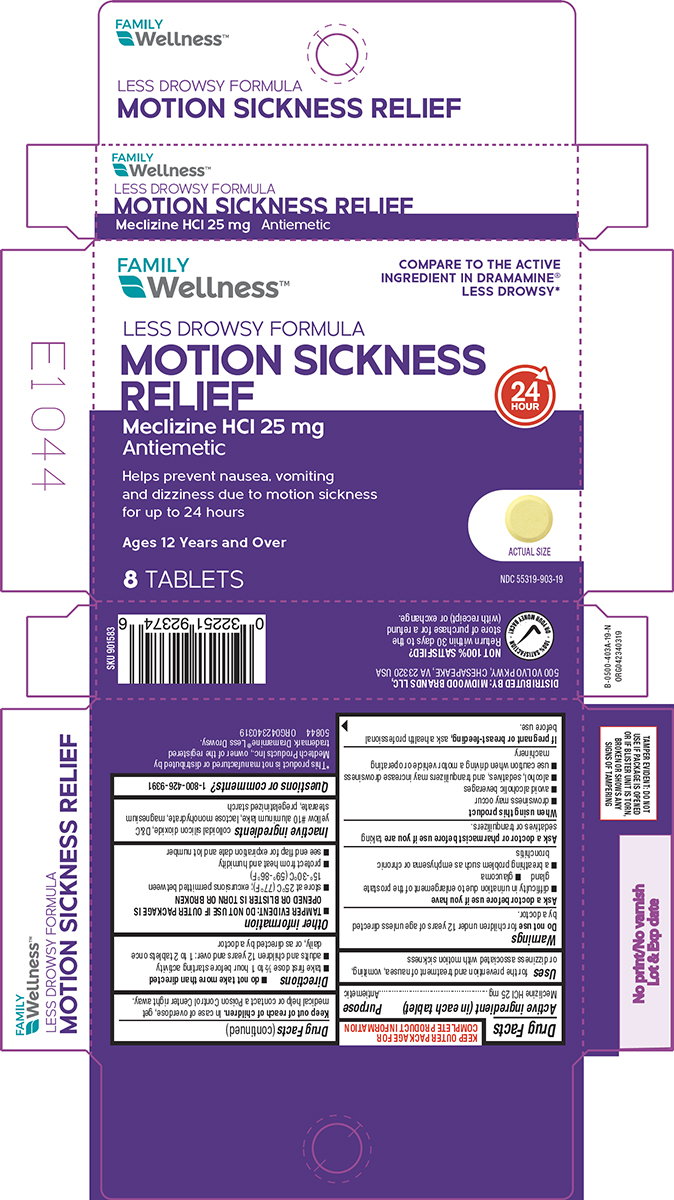 DRUG LABEL: Motion Sickness Relief
NDC: 55319-903 | Form: TABLET
Manufacturer: Family Dollar Services Inc
Category: otc | Type: HUMAN OTC DRUG LABEL
Date: 20260105

ACTIVE INGREDIENTS: MECLIZINE HYDROCHLORIDE 25 mg/1 1
INACTIVE INGREDIENTS: SILICON DIOXIDE; D&C YELLOW NO. 10 ALUMINUM LAKE; LACTOSE MONOHYDRATE; MAGNESIUM STEARATE; STARCH, CORN

Family Wellness 44-403A

Active ingredient (in each tablet)

Meclizine HCl 25 mg

Purpose

Antiemetic

Uses

for the prevention and treatment of nausea, vomiting, or dizziness associated with motion sickness

Warnings

Do not use

for children under 12 years of age unless directed by a doctor.

Ask a doctor before use if you have

- difficulty in urination due to enlargement of the prostate gland
- glaucoma
- a breathing problem such as emphysema or chronic bronchitis

Ask a doctor or pharmacist before use if you are

taking sedatives or tranquilizers.

When using this product

- drowsiness may occur
- avoid alcoholic beverages
- alcohol, sedatives, and tranquilizers may increase drowsiness
- use caution when driving a motor vehicle or operating machinery

If pregnant or breast-feeding,

ask a health professional before use.

Keep out of reach of children.

In case of overdose, get medical help or contact a Poison Control Center right away.

Directions

- do not take more than directed
- take first dose 1/2 to 1 hour before starting activity
- adults and children 12 years and over: 1 to 2 tablets once daily, or as directed by a doctor

Other information

- TAMPER EVIDENT: DO NOT USE IF OUTER PACKAGE IS OPENED OR BLISTER IS TORN OR BROKEN
- store at 25°C (77°F); excursions permitted between 15°-30°C (59°-86°F)
- protect from heat and humidity
- see end flap for expiration date and lot number

Inactive ingredients

colloidal silicon dioxide, D&C yellow #10 aluminum lake, lactose monohydrate, magnesium stearate, pregelatinized starch

Questions or comments?

1-800-426-9391

Principal display panel

FAMILY
Wellness™

COMPARE TO THE ACTIVE
INGREDIENT IN DRAMAMINE®
LESS DROWSY*

LESS DROWSY FORMULA
MOTION SICKNESS
RELIEF
Meclizine HCl 25 mg
Antiemetic

Helps prevent nausea, vomiting
and dizziness due to motion sickness
for up to 24 hours

Ages 12 Years and Over

8 TABLETS

24
HOUR

ACTUAL SIZE

NDC 55319-903-19

TAMPER EVIDENT: DO NOT
USE IF PACKAGE IS OPENED
OR IF BLISTER UNIT IS TORN,
BROKEN OR SHOWS ANY
SIGNS OF TAMPERING

*This product is not manufactured or distributed by
Medtech Products Inc., owner of the registered
trademark Dramamine® Less Drowsy.
50844 ORG042340319

DISTRIBUTED BY: MIDWOOD BRANDS LLC,
500 VOLVO PKWY, CHESAPEAKE, VA 23320 USA

NOT 100% SATISFIED?
Return within 30 days to the
store of purchase for a refund
(with receipt) or exchange.

Family Wellness 44-403A